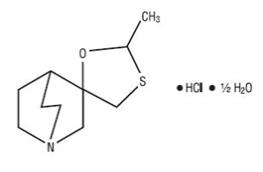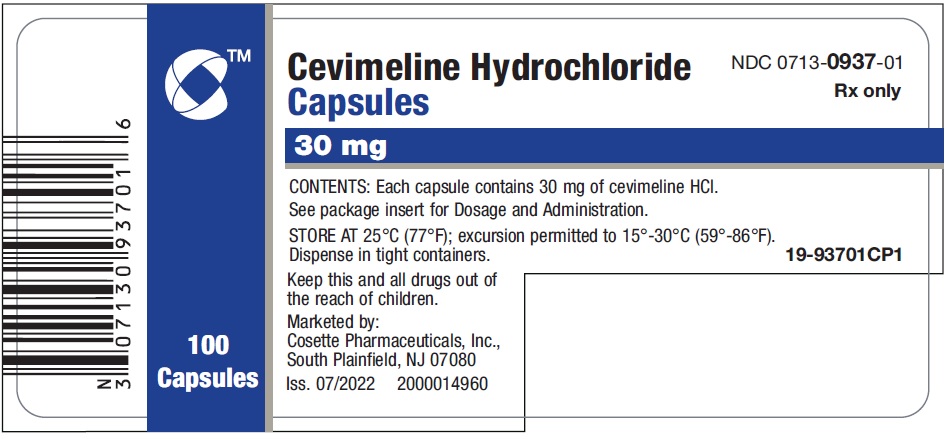 DRUG LABEL: cevimeline hydrochloride
NDC: 0713-0937 | Form: CAPSULE
Manufacturer: Cosette Pharmaceuticals, Inc.
Category: prescription | Type: HUMAN PRESCRIPTION DRUG LABEL
Date: 20230105

ACTIVE INGREDIENTS: CEVIMELINE HYDROCHLORIDE 30 mg/1 1
INACTIVE INGREDIENTS: LACTOSE MONOHYDRATE; HYDROXYPROPYL CELLULOSE, UNSPECIFIED; MAGNESIUM STEARATE

Cevimeline Hydrochloride

DESCRIPTION

Cevimeline is cis -2’-methylspiro {1-azabicyclo [2.2.2] octane-3, 5’-[1,3] oxathiolane} hydrochloride, hydrate (2:1). Its empirical formula is C10H17NOS.HCl.½ H2O, and its structural formula is:

Cevimeline has a molecular weight of 244.79. It is a white to off white crystalline powder with a melting point range of 201 to 203oC. It is freely soluble in alcohol and chloroform, very soluble in water, and virtually insoluble in ether. The pH of a 1% solution ranges from 4.6 to 5.6. Inactive ingredients include lactose monohydrate, hydroxypropyl cellulose, and magnesium stearate.

CLINICAL PHARMACOLOGY

Pharmacodynamics

Cevimeline is a cholinergic agonist which binds to muscarinic receptors. Muscarinic agonists in sufficient dosage can increase secretion of exocrine glands, such as salivary and sweat glands and increase tone of the smooth muscle in the gastrointestinal and urinary tracts.

Pharmacokinetics

Absorption: After administration of a single 30 mg capsule, cevimeline was rapidly absorbed with a mean time to peak concentration of 1.5 to 2 hours. No accumulation of active drug or its metabolites was observed following multiple dose administration. When administered with food, there is a decrease in the rate of absorption, with a fasting tMAX of 1.53 hours and a tMAX of 2.86 hours after a meal; the peak concentration is reduced by 17.3%. Single oral doses across the clinical dose range are dose proportional.

Distribution: Cevimeline has a volume of distribution of approximately 6L/kg and is <20% bound to human plasma proteins. This suggests that cevimeline is extensively bound to tissues; however, the specific binding sites are unknown.

Metabolism: Isozymes CYP2D6 and CYP3A3/4 are responsible for the metabolism of cevimeline. After 24 hours, 86.7% of the dose was recovered (16.0% unchanged, 44.5% as cis and trans-sulfoxide, 22.3% of the dose as glucuronic acid conjugate and 4% of the dose as N-oxide of cevimeline). Approximately 8% of the trans-sulfoxide metabolite is then converted into the corresponding glucuronic acid conjugate and eliminated. Cevimeline did not inhibit cytochrome P450 isozymes 1A2, 2A6, 2C9, 2C19, 2D6, 2E1, and 3A4.

Excretion: The mean half-life of cevimeline is 5+/-1hours. After 24 hours, 84% of a 30 mg dose of cevimeline was excreted in urine. After seven days, 97% of the dose was recovered in the urine and 0.5% was recovered in the feces.

Special Populations: The effects of renal impairment, hepatic impairment, or ethnicity on the pharmacokinetics of cevimeline have not been investigated.

Clinical Studies

Cevimeline has been shown to improve the symptoms of dry mouth in patients with Sjögren’s Syndrome.

A 6-week, randomized, double blind, placebo-controlled study was conducted in 75 patients
(10 men, 65 women) with a mean age of 53.6 years (range 33-75). The racial distribution was Caucasian 92%, Black 1% and other 7%. The effects of cevimeline at 30 mg tid (90 mg/day) and 60 mg tid (180 mg/day) were compared to those of placebo. Patients were evaluated by a measure called global improvement, which is defined as a response of "better" to the question, "Please rate the overall condition of your dry mouth now compared with how you felt before starting treatment in this study." Patients also had the option of selecting "worse" or "no change" as answers. Seventy-six percent of the patients in the 30 mg tid group reported a global improvement in their dry mouth symptoms compared to 35% of the patients in the placebo group. This difference was statistically significant at p=0.0043. There was no evidence that patients in the 60 mg tid group had better global evaluation scores than the patients in the 30 mg tid group.

A 12-week, randomized, double-blind, placebo-controlled study was conducted in 197 patients (10 men, 187 women) with a mean age of 54.5 years (range 23-74). The racial distribution was Caucasian 91.4%, Black 3% and other 5.6%. The effects of cevimeline at 15 mg tid (45 mg/day) and 30 mg tid (90 mg/day) were compared to those of placebo. Statistically significant global improvement in the symptoms of dry mouth (p=0.0004) was seen for the 30 mg tid group compared to placebo, but not for the 15 mg group compared to placebo. Salivary flow showed statistically significant increases at both doses of cevimeline during the study compared to placebo.

A second 12-week, randomized, double-blind, placebo-controlled study was conducted in 212 patients (11 men, 201 women) with a mean age of 55.3 years (range 24-75). The racial distribution was Caucasian 88.7%, Black 1.9% and other 9.4%. The effects of cevimeline at 15 mg tid (45 mg/day) and 30 mg tid (90 mg/day) were compared to those of placebo. No statistically significant differences were noted in the patient global evaluations. However, there was a higher placebo response rate in this study compared to the aforementioned studies. The 30 mg tid group showed a statistically significant increase in salivary flow from pre-dose to
post-dose compared to placebo (p=0.0017).

INDICATIONS AND USAGE

Cevimeline is indicated for the treatment of symptoms of dry mouth in patients with Sjögren’s Syndrome.

CONTRAINDICATIONS

Cevimeline is contraindicated in patients with uncontrolled asthma, known hypersensitivity to cevimeline, and when miosis is undesirable, e.g., in acute iritis and in narrow-angle (angle-closure) glaucoma.

WARNINGS

Cardiovascular Disease:

Cevimeline can potentially alter cardiac conduction and/or heart rate. Patients with significant cardiovascular disease may potentially be unable to compensate for transient changes in hemodynamics or rhythm induced by cevimeline. Cevimeline should be used with caution and under close medical supervision in patients with a history of cardiovascular disease evidenced by angina pectoris or myocardial infarction.

Pulmonary Disease:

Cevimeline can potentially increase airway resistance, bronchial smooth muscle tone, and bronchial secretions. Cevimeline should be administered with caution and with close medical supervision to patients with controlled asthma, chronic bronchitis, or chronic obstructive pulmonary disease.

Ocular:

Ophthalmic formulations of muscarinic agonists have been reported to cause visual blurring which may result in decreased visual acuity, especially at night and in patients with central lens changes, and to cause impairment of depth perception. Caution should be advised while driving at night or performing hazardous activities in reduced lighting.

PRECAUTIONS

General:

Cevimeline toxicity is characterized by an exaggeration of its parasympathomimetic effects. These may include: headache, visual disturbance, lacrimation, sweating, respiratory distress, gastrointestinal spasm, nausea, vomiting, diarrhea, atrioventricular block, tachycardia, bradycardia, hypotension, hypertension, shock, mental confusion, cardiac arrhythmia, and tremors.

Cevimeline should be administered with caution to patients with a history of nephrolithiasis or cholelithiasis. Contractions of the gallbladder or biliary smooth muscle could precipitate complications such as cholecystitis, cholangitis and biliary obstruction. An increase in the ureteral smooth muscle tone could theoretically precipitate renal colic or ureteral reflux in patients with nephrolithiasis.

Information for Patients:

Patients should be informed that cevimeline may cause visual disturbances, especially at night, that could impair their ability to drive safely.

If a patient sweats excessively while taking cevimeline, dehydration may develop. The patient should drink extra water and consult a health care provider.

Drug Interactions:

Cevimeline should be administered with caution to patients taking beta adrenergic antagonists, because of the possibility of conduction disturbances. Drugs with parasympathomimetic effects administered concurrently with cevimeline can be expected to have additive effects. Cevimeline might interfere with desirable antimuscarinic effects of drugs used concomitantly.

Drugs which inhibit CYP2D6 and CYP3A3/4 also inhibit the metabolism of cevimeline. Cevimeline should be used with caution in individuals known or suspected to be deficient in CYP2D6 activity, based on previous experience, as they may be at a higher risk of adverse events. In an in vitro study, cytochrome P450 isozymes 1A2, 2A6, 2C9, 2C19, 2D6, 2E1, and 3A4 were not inhibited by exposure to cevimeline.

Carcinogenesis, Mutagenesis and Impairment of Fertility:

Lifetime carcinogenicity studies were conducted in CD-1 mice and F-344 rats. A statistically significant increase in the incidence of adenocarcinomas of the uterus was observed in female rats that received cevimeline at a dosage of 100 mg/kg/day (approximately 8 times the maximum human exposure based on comparison of AUC data). No other significant differences in tumor incidence were observed in either mice or rats.

Cevimeline exhibited no evidence of mutagenicity or clastogenicity in a battery of assays that included an Ames test, an in vitro chromosomal aberration study in mammalian cells, a mouse lymphoma study in L5178Y cells, or a micronucleus assay conducted in vivo in ICR mice.

Cevimeline did not adversely affect the reproductive performance or fertility of male Sprague-Dawley rats when administered for 63 days prior to mating and throughout the period of mating at dosages up to 45 mg/kg/day (approximately 5 times the maximum recommended dose for a 60 kg human following normalization of the data on the basis of body surface area estimates). Females that were treated with cevimeline at dosages up to 45 mg/kg/day from 14 days prior to mating through day seven of gestation exhibited a statistically significantly smaller number of implantations than did control animals.

Pregnancy:

Cevimeline was associated with a reduction in the mean number of implantations when given to pregnant Sprague-Dawley rats from 14 days prior to mating through day seven of gestation at a dosage of 45 mg/kg/day (approximately 5 times the maximum recommended dose for a 60 kg human when compared on the basis of body surface area estimates). This effect may have been secondary to maternal toxicity. There are no adequate and well-controlled studies in pregnant women. Cevimeline should be used during pregnancy only if the potential benefit justifies the potential risk to the fetus.

Nursing Mothers:

It is not known whether this drug is secreted in human milk. Because many drugs are excreted in human milk, and because of the potential for serious adverse reactions in nursing infants from cevimeline, a decision should be made whether to discontinue nursing or discontinue the drug, taking into account the importance of the drug to the mother.

Pediatric Use:

Safety and effectiveness in pediatric patients have not been established.

Geriatric Use:

Although clinical studies of cevimeline included subjects over the age of 65, the numbers were not sufficient to determine whether they respond differently from younger subjects. Special care should be exercised when cevimeline treatment is initiated in an elderly patient, considering the greater frequency of decreased hepatic, renal, or cardiac function, and of concomitant disease or other drug therapy in the elderly.

ADVERSE REACTIONS

Cevimeline was administered to 1777 patients during clinical trials worldwide, including Sjögren’s patients and patients with other conditions. In placebo-controlled Sjögren’s studies in the U.S., 320 patients received cevimeline doses ranging from 15 mg tid to 60 mg tid, of whom 93% were women and 7% were men. Demographic distribution was 90% Caucasian, 5% Hispanic, 3% Black and 2% of other origin. In these studies, 14.6% of patients discontinued treatment with cevimeline due to adverse events.

The following adverse events associated with muscarinic agonism were observed in the clinical trials of cevimeline in Sjögren’s syndrome patients:

Adverse Event | Cevimeline 30 mg (tid) n*=533 | Placebo (tid) n=164
Excessive Sweating | 18.7% | 2.4%
Nausea | 13.8% | 7.9%
Rhinitis | 11.2% | 5.4%
Diarrhea | 10.3% | 10.3%
Excessive Salivation | 2.2% | 0.6%
Urinary Frequency | 0.9% | 1.8%
Asthenia | 0.5% | 0.0%
Flushing | 0.3% | 0.6%
Polyuria | 0.1% | 0.6%

* n is the total number of patients exposed to the dose at any time during the study.

In addition, the following adverse events (≥3% incidence) were reported in the Sjögren’s clinical trials:

Adverse Event | Cevimeline 30 mg (tid) n*=533 | Placebo (tid) n=164
Headache | 14.4% | 20.1%
Sinusitis | 12.3% | 10.9%
Upper Respiratory Tract Infection | 11.4% | 9.1%
Dyspepsia | 7.8% | 8.5%
Abdominal Pain | 7.6% | 6.7%
Urinary Tract Infection | 6.1% | 3.0%
Coughing | 6.1% | 3.0%
Pharyngitis | 5.2% | 5.4%
Vomiting | 4.6% | 2.4%
Injury | 4.5% | 2.4%
Back Pain | 4.5% | 4.2%
Rash | 4.3% | 6.0%
Conjunctivitis | 4.3% | 3.6%
Dizziness | 4.1% | 7.3%
Bronchitis | 4.1% | 1.2%
Arthralgia | 3.7% | 1.8%
Surgical Intervention | 3.3% | 3.0%
Fatigue | 3.3% | 1.2%
Pain | 3.3% | 3.0%
Skeletal Pain | 2.8% | 1.8%
Insomnia | 2.4% | 1.2%
Hot Flushes | 2.4% | 0.0%
Rigors | 1.3% | 1.2%
Anxiety | 1.3% | 1.2%

* n is the total number of patients exposed to the dose at any time during the study.

The following events were reported in Sjögren’s patients at incidences of <3% and ≥1%: constipation, tremor, abnormal vision, hypertonia, peripheral edema, chest pain, myalgia, fever, anorexia, eye pain, earache, dry mouth, vertigo, salivary gland pain, pruritus, influenza-like symptoms, eye infection, post operative pain, vaginitis, skin disorder, depression, hiccup, hyporeflexia, infection, fungal infection, sialoadenitis, otitis media, erythematous rash, pneumonia, edema, salivary gland enlargement, allergy, gastroesophageal reflux, eye abnormality, migraine, tooth disorder, epistaxis, flatulence, toothache, ulcerative stomatitis, anemia, hypoesthesia, cystitis, leg cramps, abscess, eructation, moniliasis, palpitation, increased amylase, xerophthalmia, allergic reaction.

The following events were reported rarely in treated Sjögren’s patients (<1%): Causal relation is unknown:

Body as a Whole Disorders: aggravated allergy, precordial chest pain, abnormal crying, hematoma, leg pain, edema, periorbital edema, activated pain trauma, pallor, changed sensation temperature, weight decrease, weight increase, choking, mouth edema, syncope, malaise, face edema, substernal chest pain

Cardiovascular Disorders: abnormal ECG, heart disorder, heart murmur, aggravated hypertension, hypotension, arrhythmia, extrasystoles, t wave inversion, tachycardia, supraventricular tachycardia, angina pectoris, myocardial infarction, pericarditis, pulmonary embolism, peripheral ischemia, superficial phlebitis, purpura, deep thrombophlebitis, vascular disorder, vasculitis, hypertension

Digestive Disorders: appendicitis, increased appetite, ulcerative colitis, diverticulitis, duodenitis, dysphagia, enterocolitis, gastric ulcer, gastritis, gastroenteritis, gastrointestinal hemorrhage, gingivitis, glossitis, rectum hemorrhage, hemorrhoids, ileus, irritable bowel syndrome, melena, mucositis, esophageal stricture, esophagitis, oral hemorrhage, peptic ulcer, periodontal destruction, rectal disorder, stomatitis, tenesmus, tongue discoloration, tongue disorder, geographic tongue, tongue ulceration, dental caries

Endocrine Disorders: increased glucocorticoids, goiter, hypothyroidism

Hematologic Disorders: thrombocytopenic purpura, thrombocythemia, thrombocytopenia, hypochromic anemia, eosinophilia, granulocytopenia, leucopenia, leukocytosis, cervical lymphadenopathy, lymphadenopathy

Liver and Biliary System Disorders: cholelithiasis, increased gamma-glutamyl transferase, increased hepatic enzymes, abnormal hepatic function, viral hepatitis, increased serum glutamate oxaloacetic transaminase (SGOT) (also called AST-aspartate aminotransferase), increased serum glutamate pyruvate transaminase (SGPT) (also called ALT-alanine aminotransferase)

Metabolic and Nutritional Disorders: dehydration, diabetes mellitus, hypercalcemia, hypercholesterolemia, hyperglycemia, hyperlipemia, hypertriglyceridemia, hyperuricemia, hypoglycemia, hypokalemia, hyponatremia, thirst

Musculoskeletal Disorders: arthritis, aggravated arthritis, arthropathy, femoral head avascular necrosis, bone disorder, bursitis, costochondritis, plantar fasciitis, muscle weakness, osteomyelitis, osteoporosis, synovitis, tendinitis, tenosynovitis

Neoplasms: basal cell carcinoma, squamous carcinoma

Nervous Disorders: carpal tunnel syndrome, coma, abnormal coordination, dysesthesia, dyskinesia dysphonia, aggravated multiple sclerosis, involuntary muscle contractions, neuralgia, neuropathy, paresthesia, speech disorder, agitation, confusion, depersonalization, aggravated depression, abnormal dreaming, emotional lability, manic reaction, paroniria, somnolence, abnormal thinking, hyperkinesia, hallucination

Miscellaneous Disorders: fall, food poisoning, heat stroke, joint dislocation, post-operative hemorrhage

Resistance Mechanism Disorders: cellulitis, herpes simplex, herpes zoster, bacterial infection, viral infection, genital moniliasis, sepsis

Respiratory Disorders: asthma, bronchospasm, chronic obstructive airway disease, dyspnea, hemoptysis, laryngitis, nasal ulcer, pleural effusion, pleurisy, pulmonary congestion, pulmonary fibrosis, respiratory disorder

Rheumatologic Disorders: aggravated rheumatoid arthritis, lupus erythematosus rash, lupus erythematosus syndrome

Skin and Appendages Disorders: acne, alopecia, burn, dermatitis, contact dermatitis, lichenoid dermatitis, eczema, furunculosis, hyperkeratosis, lichen planus, nail discoloration, nail disorder, onychia, onychomycosis, paronychia, photosensitivity reaction, rosacea, scleroderma, seborrhea, skin discoloration, dry skin, skin exfoliation, skin hypertrophy, skin ulceration, urticaria, verruca, bullous eruption, cold clammy skin

Special Senses Disorders: deafness, decreased hearing, motion sickness, parosmia, taste perversion, blepharitis, cataract, corneal opacity, corneal ulceration, diplopia, glaucoma, anterior chamber eye hemorrhage, keratitis, keratoconjunctivitis, mydriasis, myopia, photopsia, retinal deposits, retinal disorder, scleritis, vitreous detachment, tinnitus

Urogenital Disorders: epididymitis, prostatic disorder, abnormal sexual function, amenorrhea, female breast neoplasm, malignant female breast neoplasm, female breast pain, positive cervical smear test, dysmenorrhea, endometrial disorder, intermenstrual bleeding, leukorrhea, menorrhagia, menstrual disorder, ovarian cyst, ovarian disorder, genital pruritus, uterine hemorrhage, vaginal hemorrhage, atrophic vaginitis, albuminuria, bladder discomfort, increased blood urea nitrogen, dysuria, hematuria, micturition disorder, nephrosis, nocturia, increased nonprotein nitrogen, pyelonephritis, renal calculus, abnormal renal function, renal pain, strangury, urethral disorder, abnormal urine, urinary incontinence, decreased urine flow, pyuria

In one subject with lupus erythematosus receiving concomitant multiple drug therapy, a highly elevated ALT level was noted after the fourth week of cevimeline therapy. In two other subjects receiving cevimeline in the clinical trials, very high AST levels were noted. The significance of these findings is unknown.

Additional adverse events (relationship unknown) which occurred in other clinical studies (patient population different from Sjögren’s patients) are as follows:

cholinergic syndrome, blood pressure fluctuation, cardiomegaly, postural hypotension, aphasia, convulsions, abnormal gait, hyperesthesia, paralysis, abnormal sexual function, enlarged abdomen, change in bowel habits, gum hyperplasia, intestinal obstruction, bundle branch block, increased creatine phosphokinase, electrolyte abnormality, glycosuria, gout, hyperkalemia, hyperproteinemia, increased lactic dehydrogenase (LDH), increased alkaline phosphatase, failure to thrive, abnormal platelets, aggressive reaction, amnesia, apathy, delirium, delusion, dementia, illusion, impotence, neurosis, paranoid reaction, personality disorder, hyperhemoglobinemia, apnea, atelectasis, yawning, oliguria, urinary retention, distended vein, lymphocytosis.

The following adverse reaction has been identified during post-approval use of cevimeline. Because post-marketing adverse reactions are reported voluntarily from a population of uncertain size, it is not always possible to reliably estimate their frequency or establish a causal relationship to drug exposure.

Post-Marketing Adverse Events: Liver and Biliary System Disorders: cholecystitis

To report SUSPECTED ADVERSE REACTIONS, contact Cosette Pharmaceuticals, Inc. at 1-800-922-1038 or FDA at 1-800-FDA-1088 or www.fda.gov/medwatch

MANAGEMENT OF OVERDOSE

Management of the signs and symptoms of acute overdosage should be handled in a manner consistent with that indicated for other muscarinic agonists: general supportive measures should be instituted. If medically indicated, atropine, an anti-cholinergic agent, may be of value as an antidote for emergency use in patients who have had an overdose of cevimeline. If medically indicated, epinephrine may also be of value in the presence of severe cardiovascular depression or bronchoconstriction. It is not known if cevimeline is dialyzable.

DOSAGE AND ADMINISTRATION

The recommended dose of cevimeline hydrochloride capsules is 30 mg taken three times a day. There is insufficient safety information to support doses greater than 30 mg tid. There is also insufficient evidence for additional efficacy of cevimeline hydrochloride at doses greater than
30 mg tid.

HOW SUPPLIED

Cevimeline is available as white, hard gelatin capsules containing 30 mg of cevimeline hydrochloride. Cevimeline hydrochloride capsules have a white opaque cap and a white opaque body. The capsules are imprinted with “EVOXAC” on the cap and “30 mg” on the body with a black bar above “30 mg”. It is supplied in child resistant bottles of:

100 capsules (NDC 0713-0937-01).

Store at 25°C (77°F) excursion permitted to 15°-30°C (59°-86°F)

Rx only

Marketed by:
Cosette Pharmaceuticals, Inc.
South Plainfield, NJ 07080

8-0937CP1 Iss. 07/2022

2000014961

PRINCIPAL DISPLAY PANEL - 30 mg Capsule Bottle Label

NDC 0713- 0937-01
Rx only

Cevimeline Hydrochloride
Capsules
30 mg

100 Capsules